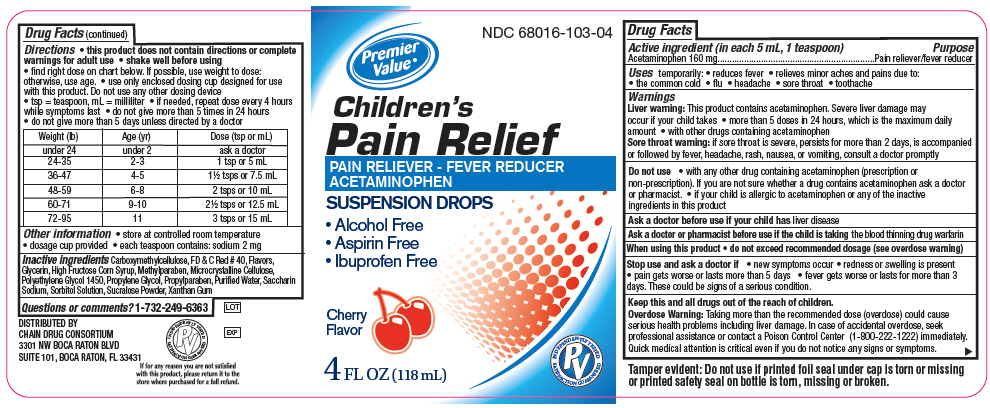 DRUG LABEL: Childrens Pain Relief
NDC: 68016-103 | Form: LIQUID
Manufacturer: Chain Drug Consortium (Premier Value)
Category: otc | Type: HUMAN OTC DRUG LABEL
Date: 20141028

ACTIVE INGREDIENTS: Acetaminophen 160 mg/5 mL
INACTIVE INGREDIENTS: Xanthan Gum; Carboxymethylcellulose; Cellulose, Microcrystalline; Methylparaben; Propylparaben; Sucralose; Saccharin Sodium; Propylene Glycol; Polyethylene Glycol 1450; High Fructose Corn syrup; Glycerin; Sorbitol; FD&C Red No. 40; Water

Children's Pain Relief

Drug Facts

Active ingredient (in each 5 mL, 1 teaspoon)

Acetaminophen 160 mg

Purpose

Pain reliever/fever reducer

Uses

temporarily:

- reduces fever
- relieves minor aches and pains due to:
  - the common cold
  - flu
  - headache
  - sore throat
  - toothache

Warnings

Liver warning

This product contains acetaminophen. Severe liver damage may occur if your child takes

- more than 5 doses in 24 hours, which is the maximum daily amount
- with other drugs containing acetaminophen

Sore throat warning: if sore throat is severe, persists for more than 2 days, is accompanied or followed by fever, headache, rash, nausea, or vomiting, consult a doctor promptly

Do not use

- with any other drug containing acetaminophen (prescription or non-prescription). If you are not sure whether a drug contains acetaminophen ask a doctor or pharmacist.
- if your child is allergic to acetaminophen or any of the inactive ingredients in this product

Ask a doctor before use if your child has liver disease

Ask a doctor or pharmacist before use if the child is taking the blood thinning drug warfarin

When using this product

- do not exceed recommended dosage (see overdose warning)

Stop use and ask a doctor if

- new symptoms occur
- redness or swelling is present
- pain gets worse or lasts more than 5 days
- fever gets worse or lasts for more than 3 days. These could be signs of a serious condition.

KEEP OUT OF REACH OF CHILDREN

Keep this and all drugs out of the reach of children.

Overdose Warning

Taking more than the recommended dose (overdose) could cause serious health problems including liver damage. In case of accidental overdose, seek professional assistance or contact a Poison Control Center (1-800-222-1222) immediately. Quick medical attention is critical even if you do not notice any signs or symptoms.

Directions

- this product does not contain directions or complete warnings for adult use
- shake well before using
- find right dose on chart below. If possible, use weight to dose: otherwise, use age.
- use only enclosed dosing cup designed for use with this product. Do not use any other dosing device
- tsp = teaspoon, mL = milliliter
- if needed, repeat dose every 4 hours while symptoms last
- do not give more than 5 times in 24 hours
- do not give more than 5 days unless directed by a doctor

Weight (lb) | Age (yr) | Dose (tsp or mL)
under 24 | under 2 | ask a doctor
24-35 | 2-3 | 1 tsp or 5 mL
36-47 | 4-5 | 1½ tsps or 7.5 mL
48-59 | 6-8 | 2 tsps or 10 mL
60-71 | 9-10 | 2½ tsps or 12.5 mL
72-95 | 11 | 3 tsps or 15 mL

Other information

- store at controlled room temperature
- dosage cup provided
- each teaspoon contains: sodium 2 mg

Inactive ingredients

Carboxymethylcellulose, FD & C Red # 40, Flavors, Glycerin, High Fructose Corn Syrup, Methylparaben, Microcrystalline Cellulose, Polyethylene Glycol 1450, Propylene Glycol, Propylparaben, Purified Water, Saccharin Sodium, Sorbitol Solution, Sucralose Powder, Xanthan Gum

Questions or comments?

1-732-249-6363

DISTRIBUTED BY
CHAIN DRUG CONSORTIUM
3301 NW BOCA RATON BLVD
SUITE 101, BOCA RATON, FL 33431

PRINCIPAL DISPLAY PANEL - 118 mL Bottle Label

NDC 68016-103-04

Premier
Value ®

Children's
Pain Relief
PAIN RELIEVER - FEVER REDUCER
ACETAMINOPHEN
SUSPENSION DROPS

- Alcohol Free
- Aspirin Free
- Ibuprofen Free

Cherry
Flavor

4 FL OZ (118 mL)

INDEPENDENTLY TESTED
PV
SATISFACTION GUARANTEED